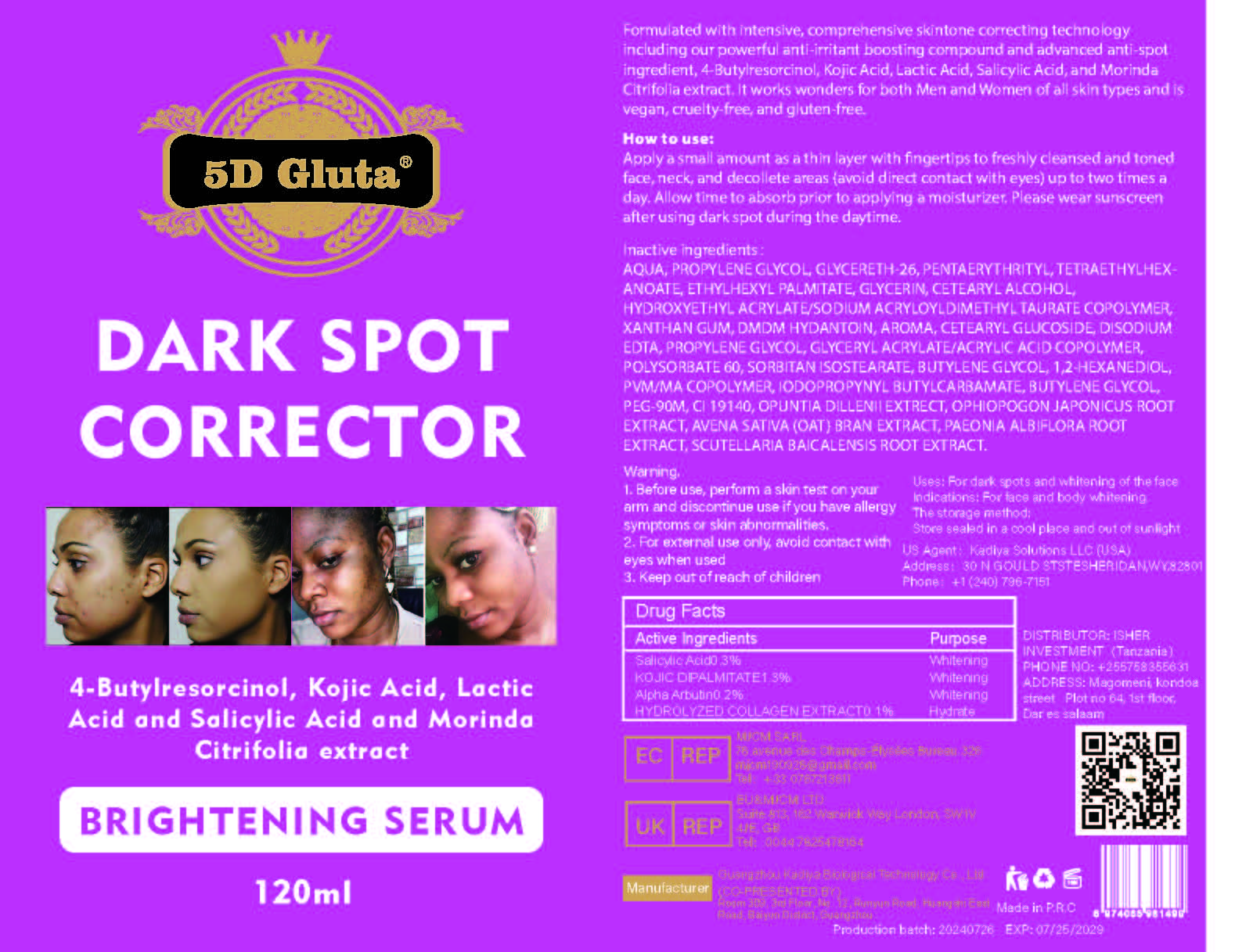 DRUG LABEL: DARK SPOT CORRECTOR SERUM
NDC: 84423-057 | Form: CREAM, AUGMENTED
Manufacturer: Guangzhou Kadiya Biotechnology Co., Ltd.
Category: otc | Type: HUMAN OTC DRUG LABEL
Date: 20241217

ACTIVE INGREDIENTS: ALPHA-ARBUTIN 0.12 g/120 mL; KOJIC DIPALMITATE 1.56 g/120 mL; SALICYLIC ACID 0.36 g/120 mL
INACTIVE INGREDIENTS: AQUA; CETEARYL ALCOHOL; PROPYLENE GLYCOL; POLYSORBATE 60; OPHIOPOGON JAPONICUS ROOT; CETEARYL GLUCOSIDE; METHYL VINYL ETHER AND MALEIC ANHYDRIDE COPOLYMER (1100000 WAMW); GLYCERETH-26; PENTAERYTHRITYL TETRAETHYLHEXANOATE; GLYCERIN; GLYCERYL ACRYLATE/ACRYLIC ACID COPOLYMER (300000 CP AT 2%); BUTYLENE GLYCOL; 1,2-HEXANEDIOL; IODOPROPYNYL BUTYLCARBAMATE; PEG-90M; CI 19140; HYDROXYETHYL ACRYLATE/SODIUM ACRYLOYLDIMETHYL TAURATE COPOLYMER (45000 MPA.S AT 1%); ETHYLHEXYL PALMITATE; SCUTELLARIA BAICALENSIS ROOT; XANTHAN GUM; DMDM HYDANTOIN; EDETATE DISODIUM; AVENA SATIVA (OAT) BRAN; PAEONIA LACTIFLORA ROOT; SORBITAN ISOSTEARATE

PURPOSE

For dark spots and whitening of the face
Indications: For face and body whitening

INACTIVE INGREDIENT

AQUA、PROPYLENE GLYCOL、GLYCERETH-26、PENTAERYTHRITYL、TETRAETHYLHEXANOATE、ETHYLHEXYL PALMITATE、GLYCERIN、CETEARYL ALCOHOL、HYDROXYETHYL ACRYLATE/SODIUM ACRYLOYLDIMETHYL TAURATE COPOLYMER、XANTHAN GUM、DMDM HYDANTOIN、AROMA、CETEARYL GLUCOSIDE、DISODIUM EDTA、PROPYLENE GLYCOL、GLYCERYL ACRYLATE/ACRYLIC ACID COPOLYMER、POLYSORBATE 60、SORBITAN ISOSTEARATE、BUTYLENE GLYCOL、1,2-HEXANEDIOL、PVM/MA COPOLYMER、IODOPROPYNYL BUTYLCARBAMATE、BUTYLENE GLYCOL、PEG-90M、CI 19140、OPUNTIA DILLENII EXTRECT、OPHIOPOGON JAPONICUS ROOT EXTRACT、AVENA SATIVA (OAT) BRAN EXTRACT、PAEONIA ALBIFLORA ROOT EXTRACT、SCUTELLARIA BAICALENSIS ROOT EXTRACT

WARNINGS

1.Before use, perform a skin test on your arm and discontinue use if you have allergy symptoms or skin abnormalities.
2、For external use only, avoid contact with eyes when used
3、Keep out of reach of children

INDICATIONS AND USAGE

Formulated with intensive, comprehensive skintone correcting technology including our powerful anti-irritant boosting compound and advanced anti-spot ingredient, 4-Butylresorcinol, Kojic Acid, Lactic Acid, Salicylic Acid, and Morinda Citrifolia extract. It works wonders for both Men and Women of all skin types and is vegan, cruelty-free, and gluten-free.

DOSAGE AND ADMINISTRATION

Apply a small amount as a thin layer with fingertips to freshly cleansed and toned face, neck, and decollete areas (avoid direct contact with eyes) up to two times a day. Allow time to absorb prior to applying a moisturizer. Please wear sunscreen after using dark spot during the daytime.

KEEP OUT OF REACH OF CHILDREN SECTION

Active Ingredients Purpose
Salicylic Acid0.3% Whitening
KOJIC DIPALMITATE1.3% Whitening
Alpha Arbutin0.2% Whitening
HYDROLYZED COLLAGEN EXTRACT0.1% hydrate

PACKAGE LABEL

Active Ingredients Purpose
Salicylic Acid0.3% Whitening
KOJIC DIPALMITATE1.3% Whitening
Alpha Arbutin0.2% Whitening
HYDROLYZED COLLAGEN EXTRACT0.1% hydrate

Uses：
For dark spots and whitening of the face
Indications: For face and body whitening
The storage method：
Store sealed in a cool place and out of sunlight

Warning.
1.Before use, perform a skin test on your arm and discontinue use if you have allergy symptoms or skin abnormalities.
2、For external use only, avoid contact with eyes when used
3、Keep out of reach of children

Inactive ingredients：
AQUA、PROPYLENE GLYCOL、GLYCERETH-26、PENTAERYTHRITYL、TETRAETHYLHEXANOATE、ETHYLHEXYL PALMITATE、GLYCERIN、CETEARYL ALCOHOL、HYDROXYETHYL ACRYLATE/SODIUM ACRYLOYLDIMETHYL TAURATE COPOLYMER、XANTHAN GUM、DMDM HYDANTOIN、AROMA、CETEARYL GLUCOSIDE、DISODIUM EDTA、PROPYLENE GLYCOL、GLYCERYL ACRYLATE/ACRYLIC ACID COPOLYMER、POLYSORBATE 60、SORBITAN ISOSTEARATE、BUTYLENE GLYCOL、1,2-HEXANEDIOL、PVM/MA COPOLYMER、IODOPROPYNYL BUTYLCARBAMATE、BUTYLENE GLYCOL、PEG-90M、CI 19140、OPUNTIA DILLENII EXTRECT、OPHIOPOGON JAPONICUS ROOT EXTRACT、AVENA SATIVA (OAT) BRAN EXTRACT、PAEONIA ALBIFLORA ROOT EXTRACT、SCUTELLARIA BAICALENSIS ROOT EXTRACT